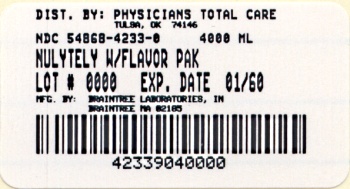 DRUG LABEL: NuLYTELY
NDC: 54868-4233 | Form: POWDER, FOR SOLUTION
Manufacturer: Physicians Total Care, Inc.
Category: prescription | Type: HUMAN PRESCRIPTION DRUG LABEL
Date: 20091015

ACTIVE INGREDIENTS: POLYETHYLENE GLYCOL 3350 210 g/2 L; SODIUM BICARBONATE 2.86 g/2 L; SODIUM CHLORIDE 5.6 g/2 L; POTASSIUM CHLORIDE 0.74 g/2 L
INACTIVE INGREDIENTS: CHERRY; ORANGE; PINEAPPLE; LEMON; LIME

NuLYTELY® with Flavor Packs
PEG-3350, Sodium Chloride, Sodium Bicarbonate and Potassium Chloride for Oral Solution

Rx only

DESCRIPTION:

A white powder for reconstitution containing 420 g polyethylene glycol 3350, 5.72 g sodium bicarbonate, 11.2 g sodium chloride, 1.48 g potassium chloride and one 2.0 g flavor pack (optional). When dissolved in water to a volume of 4 liters, NuLYTELY (PEG-3350, sodium chloride, sodium bicarbonate and potassium chloride for oral solution) is an isosmotic solution having a pleasant mineral water taste. NuLYTELY is administered orally or via nasogastric tube as a gastrointestinal lavage. NuLYTELY Flavor Packs are available in Cherry, Lemon -Lime, Orange and Pineapple. This preparation can be used without the addition of a NuLYTELY Flavor Pack.

CLINICAL PHARMACOLOGY:

NuLYTELY induces a diarrhea which rapidly cleanses the bowel, usually within four hours. The osmotic activity of polyethylene glycol 3350 and the electrolyte concentration result in virtually no net absorption or excretion of ions or water. Accordingly, large volumes may be administered without significant changes in fluid or electrolyte balance.

INDICATIONS AND USAGE:

NuLYTELY is indicated for bowel cleansing prior to colonoscopy.

CONTRAINDICATIONS:

NuLYTELY is contraindicated in patients known to be hypersensitive to any of the components. NuLYTELY is contraindicated in patients with ileus, gastrointestinal obstruction, gastric retention, bowel perforation, toxic colitis or toxic megacolon.

WARNINGS:

NuLYTELY Flavor Packs are for use only in combination with the contents of the accompanying 4 liter container. No additional ingredients, e.g. flavorings, should be added to the solution. NuLYTELY should be used with caution in patients with severe ulcerative colitis. Use of NuLYTELY in children younger than 2 years of age should be carefully monitored for occurrence of possible hypoglycemia, as this solution has no caloric substrate. Dehydration has been reported in 1 child and hypokalemia has been reported in 3 children.

PRECAUTIONS:

GENERAL PRECAUTIONS

General: Patients with impaired gag reflex, unconscious, or semiconscious patients, and patients prone to regurgitation or aspiration should be observed during the administration of NuLYTELY, especially if it is administered via nasogastric tube. If a patient experiences severe bloating, distention or abdominal pain, administration should be slowed or temporarily discontinued until the symptoms abate. If gastrointestinal obstruction or perforation is suspected, appropriate studies should be performed to rule out these conditions before administration of NuLYTELY.

PATIENT COUNSELING INFORMATION

Information for patients: NuLYTELY produces a watery stool which cleanses the bowel before examination. Prepare the solution according to the instructions on the bottle. It is more palatable if chilled. For best results, no solid food should be consumed during the 3 to 4 hour period before drinking the solution, but in no case should solid foods be eaten within 2 hours of taking NuLYTELY.

Adults drink 240 mL (8 oz.) every 10 minutes. Continue drinking until the watery stool is clear and free of solid matter. This usually requires at least 3 liters. Any unused portion should be discarded. Pediatric patients (aged 6 months or greater) drink 25 mL/kg/hour. Continue drinking until the watery stool is clear and free of solid matter. Any unused portion should be discarded. Rapid drinking of each portion is better than drinking small amounts continuously. The first bowel movement should occur approximately one hour after the start of NuLYTELY administration. You may experience some abdominal bloating and distention before the bowels start to move. If severe discomfort or distention occur, stop drinking temporarily or drink each portion at longer intervals until these symptoms disappear.

Use of NuLYTELY in children younger than 2 years of age should be carefully monitored for occurrence of possible hypoglycemia, as this solution has no caloric substrate. Dehydration has been reported in 1 child and hypokalemia has been reported in 3 children.

DRUG INTERACTIONS

Drug Interactions: Oral medication administered within one hour of the start of administration of NuLYTELY may be flushed from the gastrointestinal tract and not absorbed.

CARCINOGENESIS AND MUTAGENESIS AND IMPAIRMENT OF FERTILITY

Carcinogenesis, Mutagenesis, Impairment of Fertility: Carcinogenic and reproductive studies with animals have not been performed.

PREGNANCY

Pregnancy: Category C. Animal reproduction studies have not been conducted with NuLYTELY. It is also not known whether NuLYTELY can cause fetal harm when administered to a pregnant woman or can affect reproductive capacity. NuLYTELY should be given to a pregnant woman only if clearly needed.

PEDIATRIC USE

Pediatric Use: Safety and effectiveness of NuLYTELY in pediatric patients aged 6 months and older is supported by evidence from adequate and well-controlled clinical trials of NuLYTELY in adults with additional safety and efficacy data from published studies of similar formulations.

ADVERSE REACTIONS:

Nausea, abdominal fullness and bloating are the most common adverse reactions (occurring in up to 50% of patients) to administration of NuLYTELY. Abdominal cramps, vomiting and anal irritation occur less frequently. These adverse reactions are transient and subside rapidly. Isolated cases of urticaria, rhinorrhea, dermatitis and (rarely) anaphylactic reaction have been reported which may represent allergic reactions.

Published literature contains isolated reports of serious adverse reaction following the administration of PEG-ELS products in patients over 60 years of age. These adverse events include upper GI bleeding from Mallory-Weiss Tear, esophageal perforation, asystole, sudden dyspnea with pulmonary edema, and “butterfly-like” infiltrate on chest X-ray after vomiting and aspirating PEG.

DOSAGE AND ADMINISTRATION:

NuLYTELY is usually administered orally, but may be given via nasogastric tube to patients who are unwilling or unable to drink the solution. Ideally, the patient should fast for approximately three or four hours prior to NuLYTELY administration, but in no case should solid food be given for at least two hours before the solution is given.

Oral administration: Adults: At a rate of 240 mL(8 oz.) every 10 minutes, until the rectal effluent is clear or 4 liters are consumed. Pediatric Patients (aged 6 months or greater): At a rate of 25 mL/kg/hour, until the rectal effluent is clear. Rapid drinking of each portion is preferred to drinking small amounts continuously. Nasogastric tube administration: Adults: At a rate of 20-30 mL per minute (1.2-1.8 liters per hour). Pediatric Patients (aged 6 months or greater): At a rate of 25 mL/kg/hour, until the rectal effluent is clear.

The first bowel movement should occur approximately one hour after the start of NuLYTELY administration. Ingestion of 4 liters of NuLYTELY solution prior to gastrointestinal examination produces satisfactory preparation in over 95% of patients.

Various regimens have been used. One method is to schedule patients for examination in midmorning or later, allowing the patients three hours for drinking and an additional one hour period for complete bowel evacuation. Another method is to administer NuLYTELY on the evening before the examination.

Preparation of the solution: NuLYTELY solution is prepared by filling the container to the 4 liter mark with water and shaking vigorously several times to insure that the ingredients are dissolved. Dissolution is facilitated by using lukewarm water. The solution is more palatable if chilled before administration. However, chilled solution is not recommended for infants. The reconstituted solution should be refrigerated and used within 48 hours. Discard any unused portion.

HOW SUPPLIED:

NuLYTELY, Cherry Flavor NuLYTELY, Lemon-Lime Flavor NuLYTELY, Orange Flavor NuLYTELY are available in a disposable jug, in powdered form, for oral administration as a solution following reconstitution.

4 liter Plastic Bottle NDC 54868-4233-0

NuLYTELY with Flavor Packs is supplied in a disposable jug, in powdered form, for oral administration as a solution following reconstitution. Each jug has an attached package containing 4 flavor packs; one each 2.0 g: Cherry, Lemon-Lime, Orange and Pineapple flavoring, in powdered form, for the addition of ONE pack by the pharmacist prior to dispensing.

Each jug contains:

NuLYTELY: polyethylene glycol 3350 420 g, sodium bicarbonate 5.72 g, sodium chloride 11.2 g, potassium chloride 1.48 g. When made up to 4 liters volume with water, the solution contains PEG-3350 31.3 mmol/L, sodium 65 mmol/L, chloride 53 mmol/L, bicarbonate 17 mmol/L and potassium 5 mmol/L.

Cherry Flavor NuLYTELY: polyethylene glycol 3350 420 g, sodium bicarbonate 5.72 g, sodium chloride 11.2 g, potassium chloride 1.48 g and flavoring ingredients 2.0 g. When made up to 4 liters volume with water, the solution contains PEG-3350 31.3 mmol/L, sodium 65 mmol/L, chloride 53 mmol/L, bicarbonate 17 mmol/L and potassium 5 mmol/L.

Lemon-Lime Flavor NuLYTELY: polyethylene glycol 3350 420 g, sodium bicarbonate 5.72 g, sodium chloride 11.2 g, potassium chloride 1.48 g and flavoring ingredients 2.0 g. When made up to 4 liters volume with water, the solution contains PEG-3350 31.3 mmol/L, sodium 65 mmol/L, chloride 53 mmol/L, bicarbonate 17 mmol/L and potassium 5 mmol/L.

Orange Flavor NuLYTELY: polyethylene glycol 3350 420 g, sodium bicarbonate 5.72 g, sodium chloride 11.2 g, potassium chloride 1.48 g and flavoring ingredients 2.0 g. When made up to 4 liters volume with water, the solution contains PEG-3350 31.3 mmol/L, sodium 65 mmol/L, chloride 53 mmol/L, bicarbonate 17 mmol/L and potassium 5 mmol/L.

NuLYTELY with Flavor Packs: polyethylene glycol 3350 420 g, sodium bicarbonate 5.72 g, sodium chloride 11.2 g, potassium chloride 1.48 g and flavoring ingredients 2.0 g (optional). When made up to 4 liters volume with water, the solution contains PEG-3350 31.3 mmol/L, sodium 65 mmol/L, chloride 53 mmol/L, bicarbonate 17 mmol/L and potassium 5 mmol/L.

STORAGE: Store at 25°C (77°F); excursions permitted to 15-30°C (59-86°F) [see USP Controlled Room Temperature]. When reconstituted, keep solution refrigerated. Use within 48 hours. Discard unused portion.

Distributed by Braintree Laboratories, Inc., Braintree, MA 02185

S 12/08

Relabeling of "Additional" label by:
Physicians Total Care, Inc.
Tulsa, OK 74146

PAKAGE LABEL – PRINCIPAL DISPLAY PANEL

NDC 54868-4233-0

NuLYTELY®

(PEG-3350, Sodium Chloride, Sodium Bicarbonate and Potassium Chloride for Oral Solution)

With Flavor Packs

Rx Only